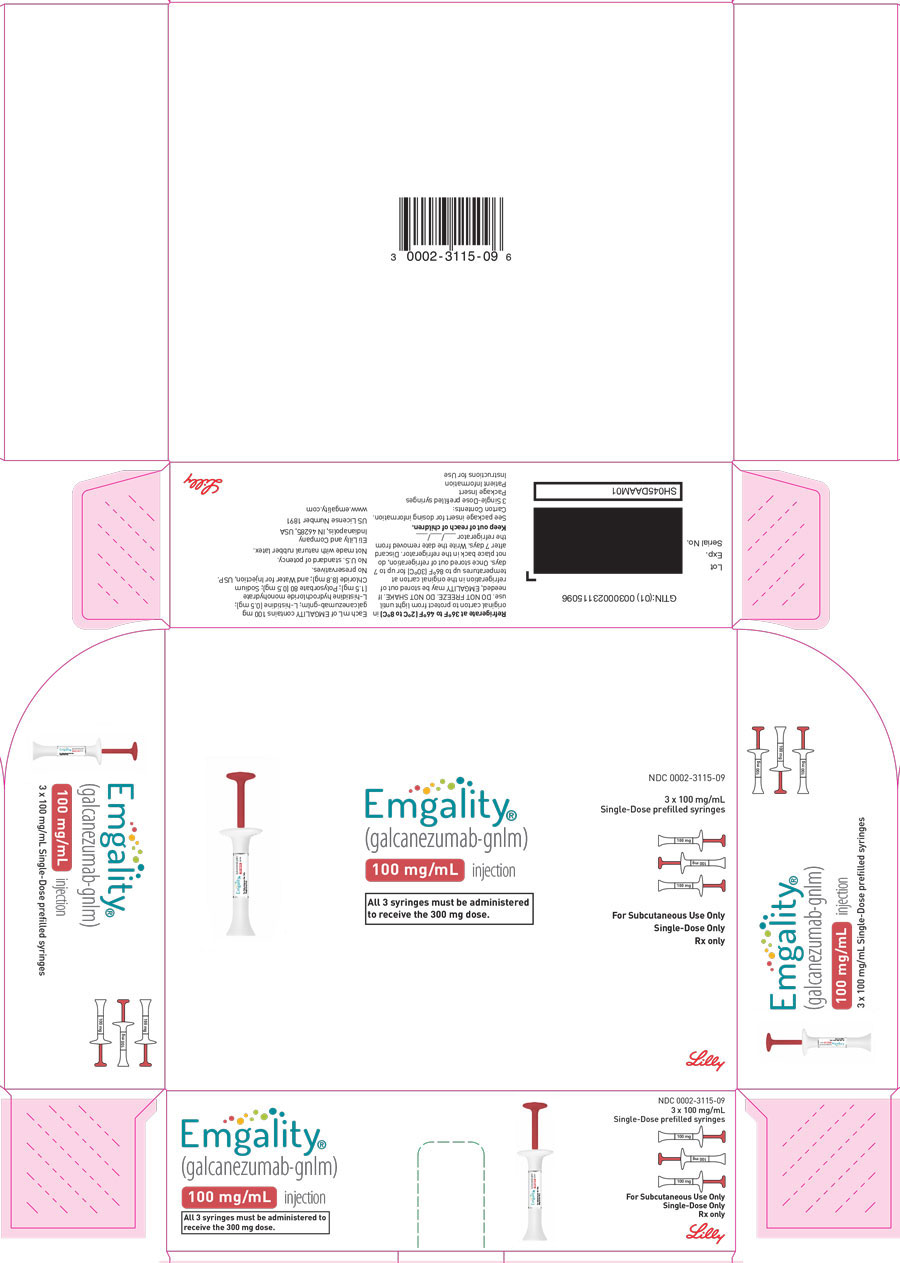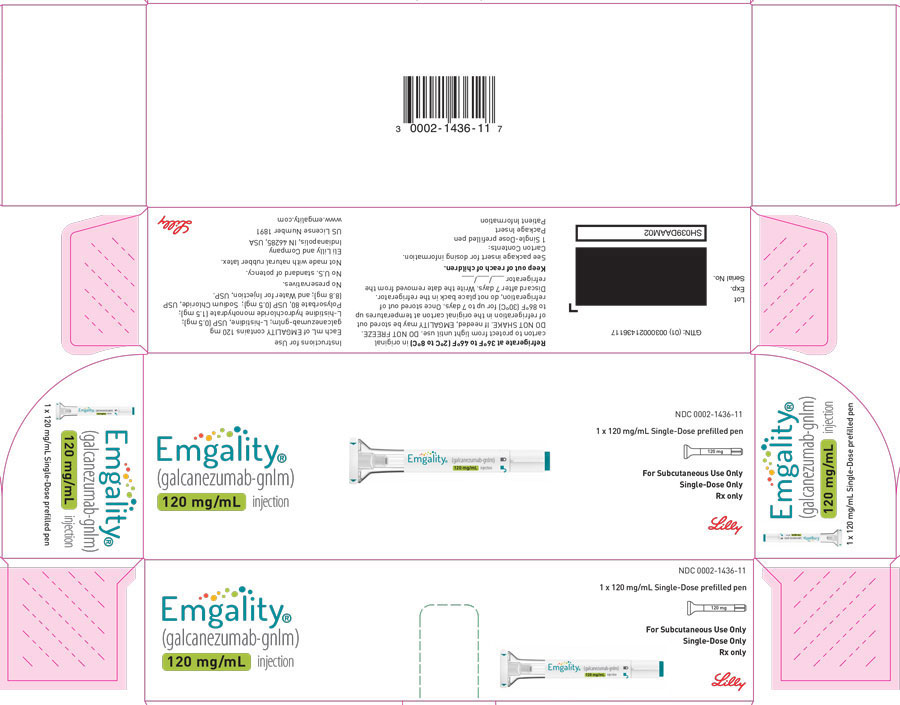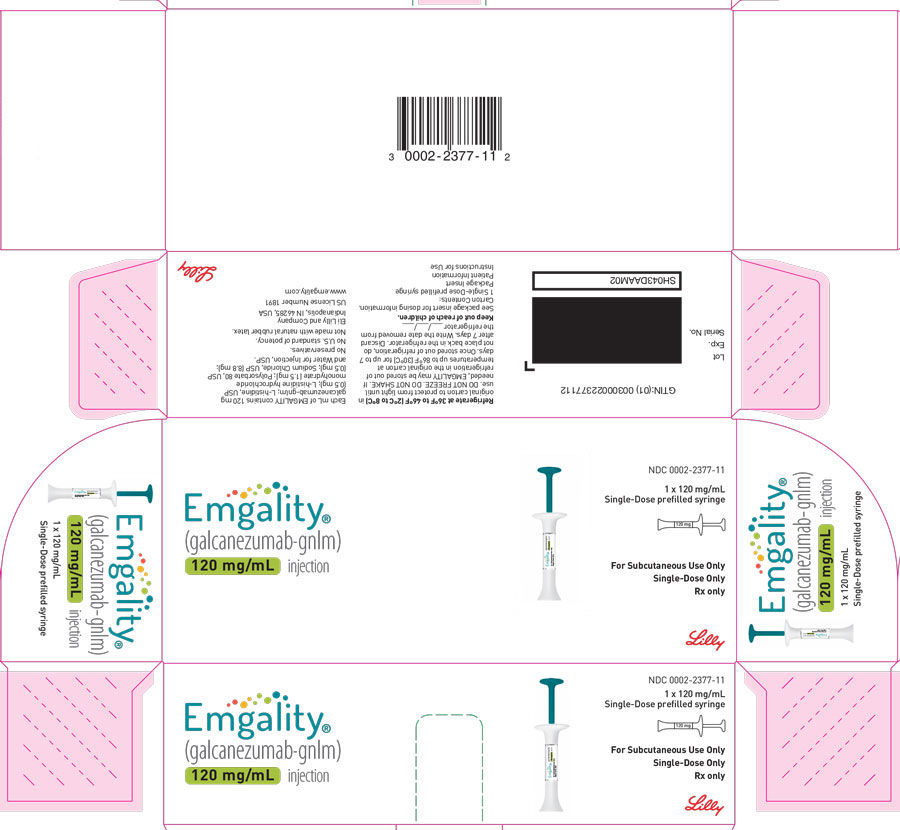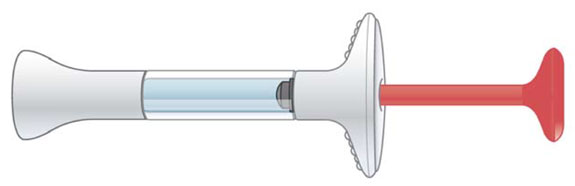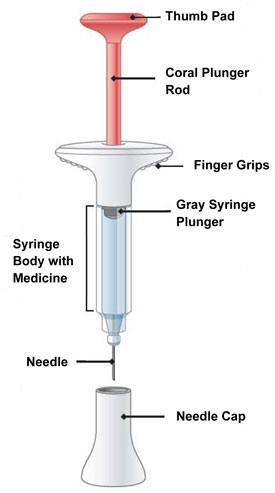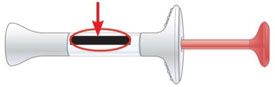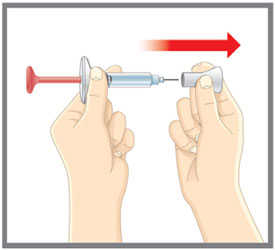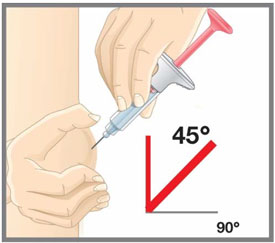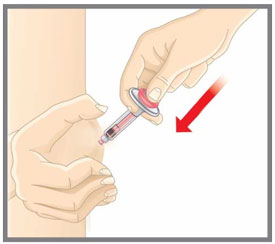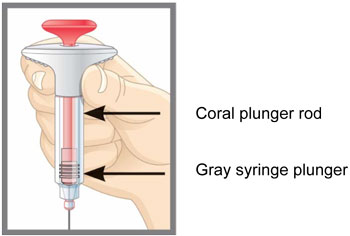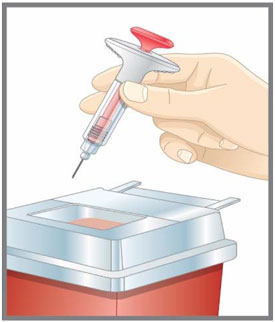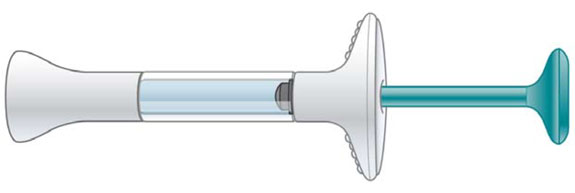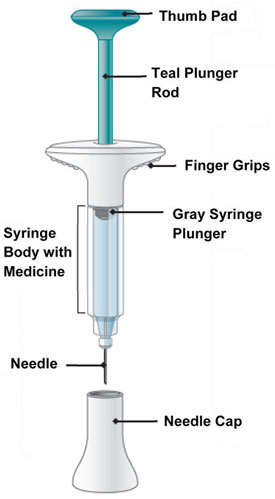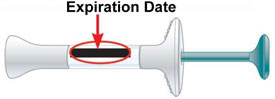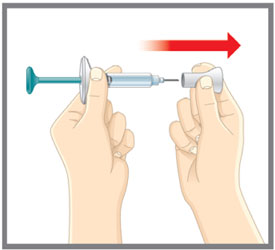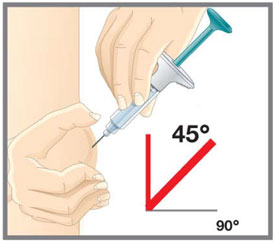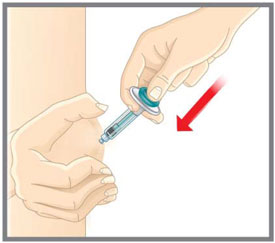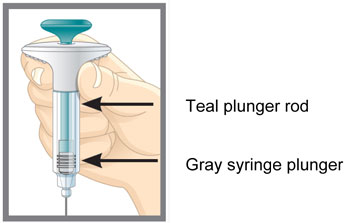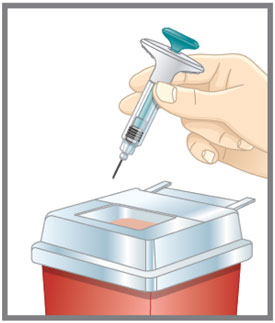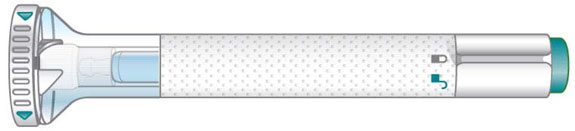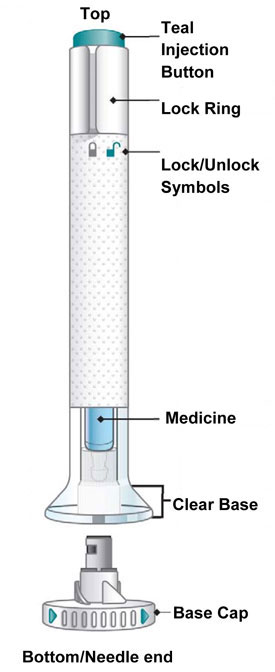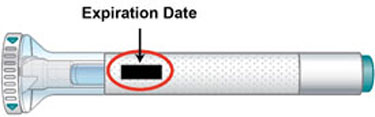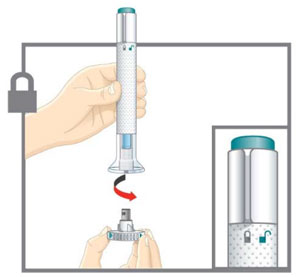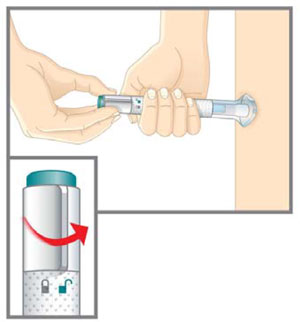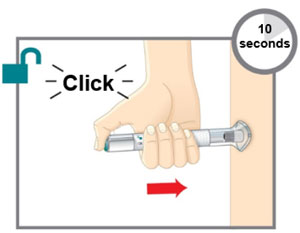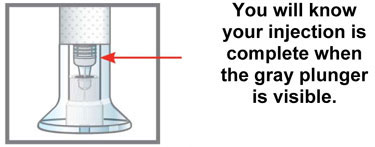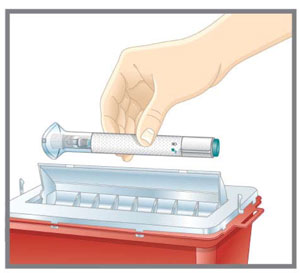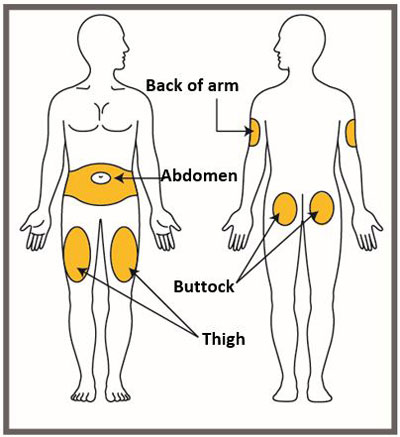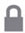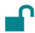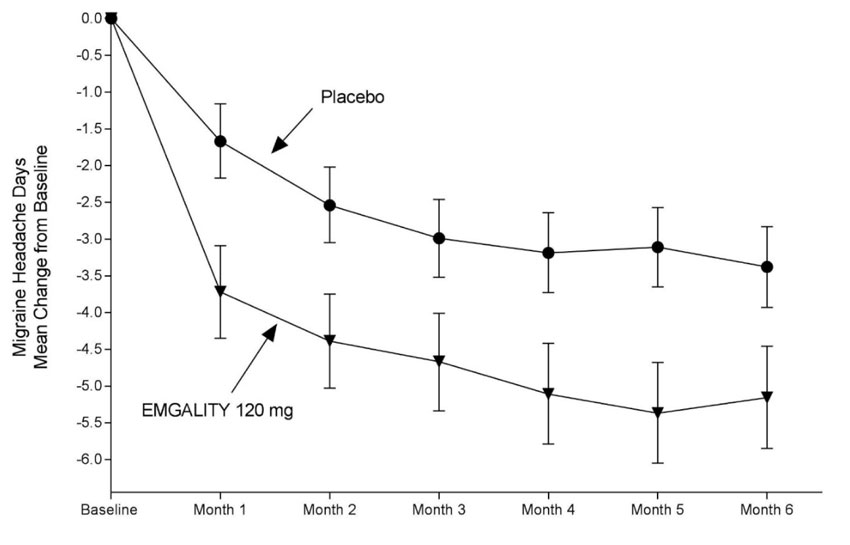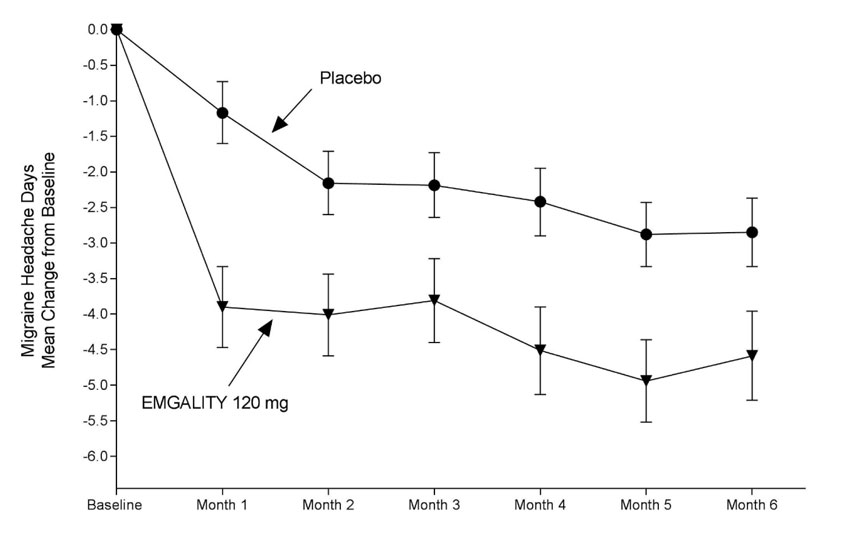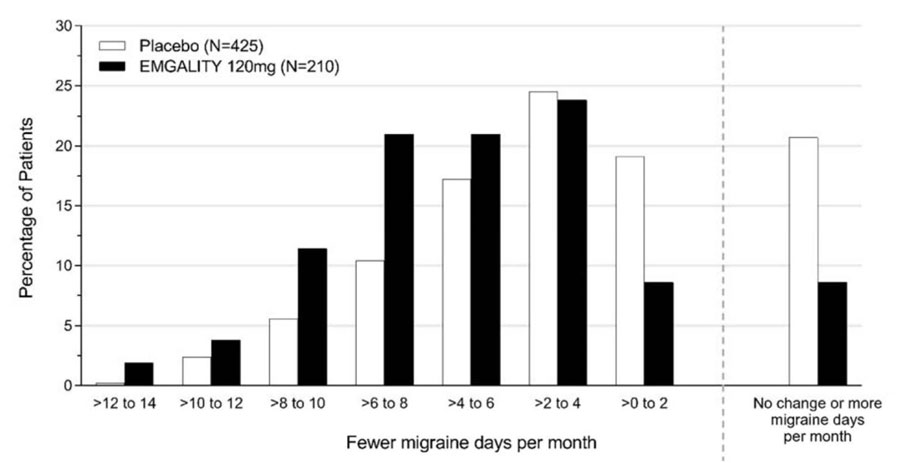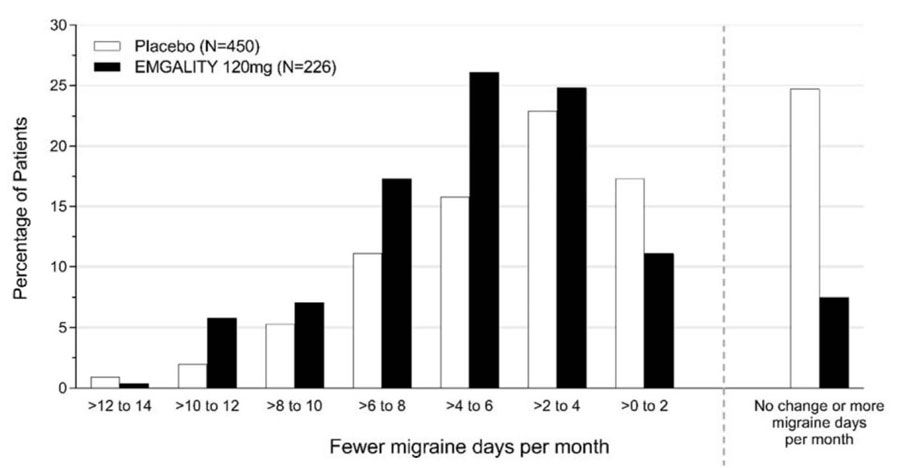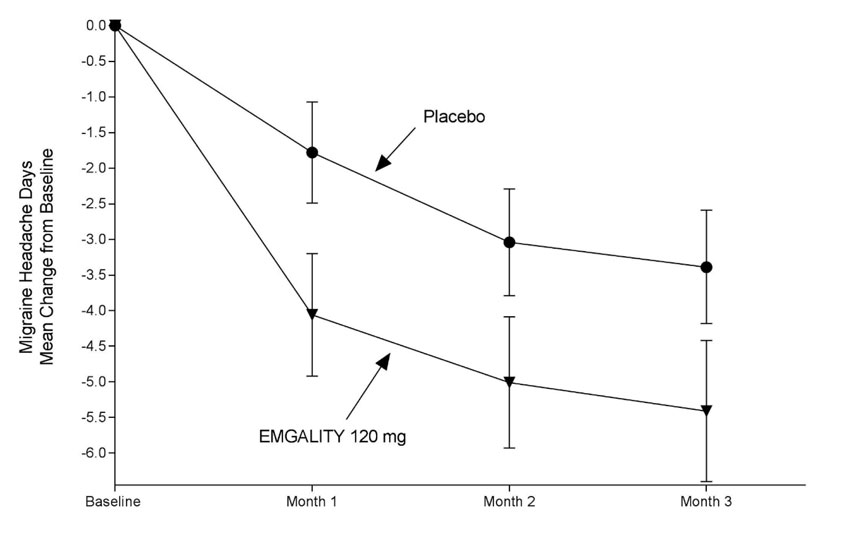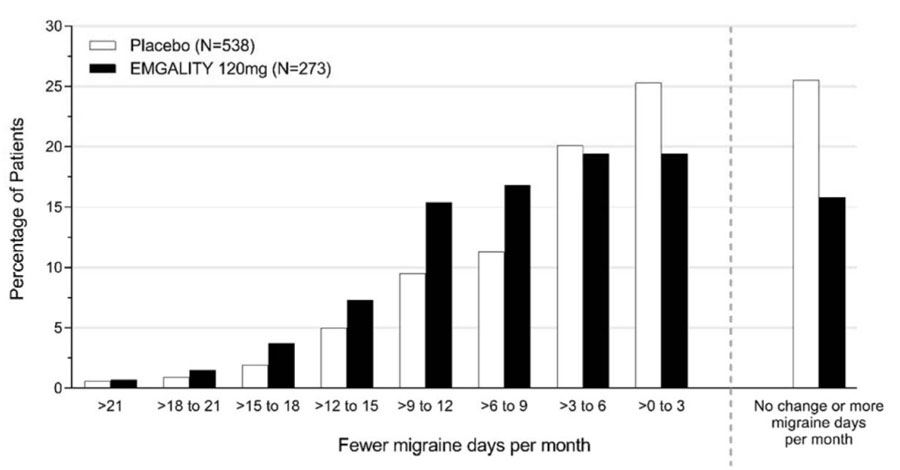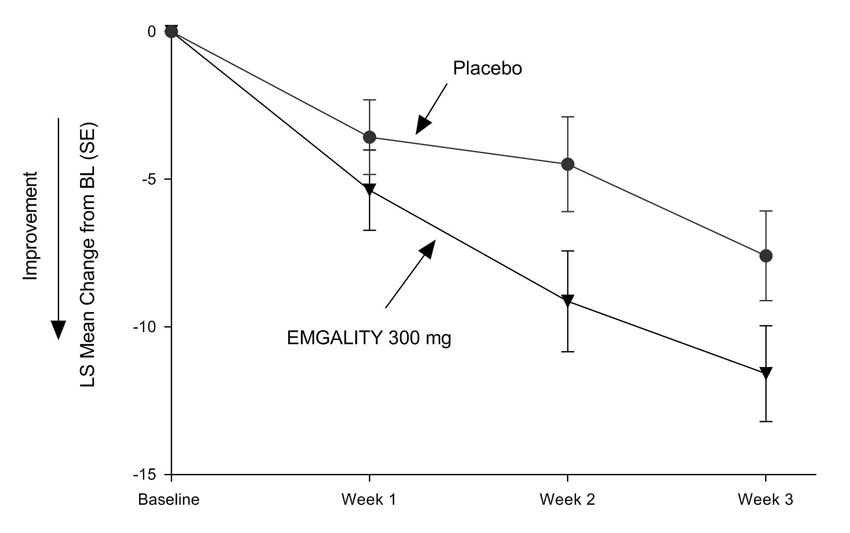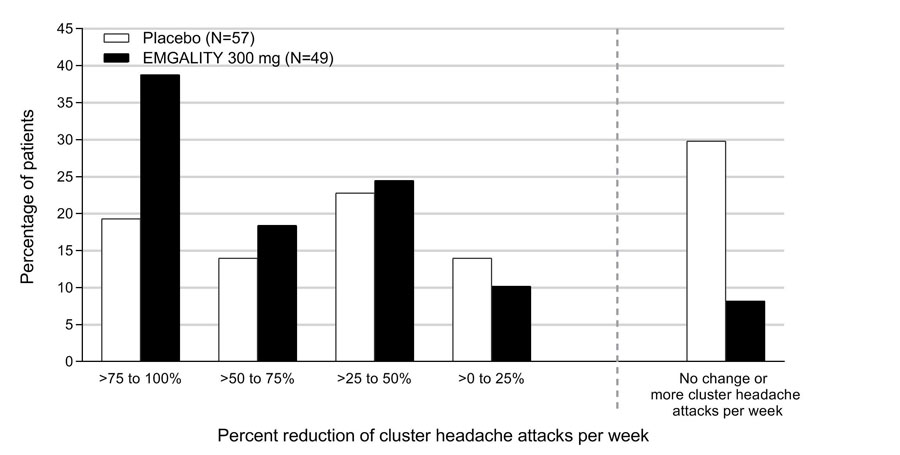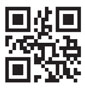 DRUG LABEL: EMGALITY
NDC: 0002-1436 | Form: INJECTION, SOLUTION
Manufacturer: Eli Lilly and Company
Category: prescription | Type: HUMAN PRESCRIPTION DRUG LABEL
Date: 20251021

ACTIVE INGREDIENTS: galcanezumab 120 mg/1 mL
INACTIVE INGREDIENTS: Histidine 0.5 mg/1 mL; Histidine Monohydrochloride Monohydrate 1.5 mg/1 mL; Sodium Chloride 8.8 mg/1 mL; Polysorbate 80 0.5 mg/1 mL; Water

HIGHLIGHTS OF PRESCRIBING INFORMATION

These highlights do not include all the information needed to use EMGALITY safely and effectively. See full prescribing information for EMGALITY.
EMGALITY (galcanezumab-gnlm) injection, for subcutaneous use
Initial U.S. Approval: 2018

RECENT MAJOR CHANGES

Warnings and Precautions (5.2, 5.3) | 03/2025

1 INDICATIONS AND USAGE

EMGALITY® is a calcitonin-gene related peptide antagonist indicated in adults for the:

- preventive treatment of migraine. (1.1)
- treatment of episodic cluster headache. (1.2)

2 DOSAGE AND ADMINISTRATION

- For subcutaneous use only. (2.1, 2.2, 2.3)
- Migraine recommended dosage: 240 mg loading dose (administered as two consecutive injections of 120 mg each), followed by monthly doses of 120 mg. (2.1)
- Episodic cluster headache recommended dosage: 300 mg (administered as three consecutive injections of 100 mg each) at the onset of the cluster period, and then monthly until the end of the cluster period. (2.2)
- Administer in the abdomen, thigh, back of the upper arm, or buttocks subcutaneously. (2.3)

3 DOSAGE FORMS AND STRENGTHS

- Injection: 120 mg/mL solution in a single-dose prefilled pen (3)
- Injection: 120 mg/mL solution in a single-dose prefilled syringe (3)
- Injection: 100 mg/mL solution in a single-dose prefilled syringe (3)

4 CONTRAINDICATIONS

EMGALITY is contraindicated in patients with serious hypersensitivity to galcanezumab-gnlm or to any of the excipients. (4)

5 WARNINGS AND PRECAUTIONS

- Hypersensitivity Reactions: If a serious hypersensitivity reaction occurs, discontinue administration of EMGALITY and initiate appropriate therapy. Hypersensitivity reactions can occur days after administration, and may be prolonged. (5.1)
- Hypertension: New-onset or worsening of pre-existing hypertension may occur. (5.2)
- Raynaud's Phenomenon: New-onset or worsening of pre-existing Raynaud's phenomenon may occur. (5.3)

6 ADVERSE REACTIONS

The most common adverse reactions (incidence ≥2% and at least 2% greater than placebo) in EMGALITY clinical studies were injection site reactions. (6.1)

To report SUSPECTED ADVERSE REACTIONS, contact Eli Lilly and Company at 1-800-LillyRx (1-800-545-5979) or FDA at 1-800-FDA-1088 or www.fda.gov/medwatch.

FULL PRESCRIBING INFORMATION

1 INDICATIONS AND USAGE

1.1 Migraine

EMGALITY is indicated for the preventive treatment of migraine in adults.

1.2 Episodic Cluster Headache

EMGALITY is indicated for the treatment of episodic cluster headache in adults.

2 DOSAGE AND ADMINISTRATION

2.1 Recommended Dosing for Migraine

The recommended dosage of EMGALITY is 240 mg (two consecutive subcutaneous injections of 120 mg each) once as a loading dose, followed by monthly doses of 120 mg injected subcutaneously.

If a dose of EMGALITY is missed, administer as soon as possible. Thereafter, EMGALITY can be scheduled monthly from the date of the last dose.

2.2 Recommended Dosing for Episodic Cluster Headache

The recommended dosage of EMGALITY is 300 mg (three consecutive subcutaneous injections of 100 mg each) at the onset of the cluster period, and then monthly until the end of the cluster period.

If a dose of EMGALITY is missed during a cluster period, administer as soon as possible. Thereafter, EMGALITY can be scheduled monthly from the date of the last dose until the end of the cluster period.

2.3 Important Administration Instructions

EMGALITY is for subcutaneous use only.

EMGALITY is intended for patient self-administration. Prior to use, provide proper training to patients and/or caregivers on how to prepare and administer EMGALITY using the single-dose prefilled pen or single-dose prefilled syringe, including aseptic technique [see How Supplied/Storage and Handling (16.2) and Instructions for Use]:

- Protect EMGALITY from direct sunlight.
- Prior to subcutaneous administration, allow EMGALITY to sit at room temperature for 30 minutes. Do not warm by using a heat source such as hot water or a microwave.
- Do not shake the product.
- Inspect EMGALITY visually for particulate matter and discoloration prior to administration, whenever solution and container permit [see Dosage Forms and Strengths (3) and How Supplied/Storage and Handling (16.1)]. Do not use EMGALITY if it is cloudy or there are visible particles.
- Administer EMGALITY in the abdomen, thigh, back of the upper arm, or buttocks subcutaneously. Do not inject into areas where the skin is tender, bruised, red, or hard.
- Both the prefilled pen and prefilled syringe are single-dose and deliver the entire contents.

3 DOSAGE FORMS AND STRENGTHS

EMGALITY is a sterile clear to opalescent, colorless to slightly yellow to slightly brown solution available as follows:

- Injection: 120 mg/mL in a single-dose prefilled pen
- Injection: 120 mg/mL in a single-dose prefilled syringe
- Injection: 100 mg/mL in a single-dose prefilled syringe

4 CONTRAINDICATIONS

EMGALITY is contraindicated in patients with serious hypersensitivity to galcanezumab-gnlm or to any of the excipients [see Warnings and Precautions (5.1)].

5 WARNINGS AND PRECAUTIONS

5.1 Hypersensitivity Reactions

Hypersensitivity reactions, including dyspnea, urticaria, and rash, have occurred with EMGALITY in clinical studies and the postmarketing setting. Cases of anaphylaxis and angioedema have also been reported in the postmarketing setting. If a serious or severe hypersensitivity reaction occurs, discontinue administration of EMGALITY and initiate appropriate therapy [see Contraindications (4), Adverse Reactions (6.1), and Patient Counseling Information (17)]. Hypersensitivity reactions can occur days after administration and may be prolonged.

5.2 Hypertension

Development of hypertension and worsening of pre-existing hypertension have been reported following the use of CGRP antagonists, including EMGALITY, in the postmarketing setting. Some of the patients who developed new-onset hypertension had risk factors for hypertension. There were cases requiring initiation of pharmacological treatment for hypertension and, in some cases, hospitalization. Hypertension may occur at any time during treatment but was most frequently reported within 7 days of therapy initiation. EMGALITY was discontinued in many of the reported cases.

Monitor patients treated with EMGALITY for new-onset hypertension or worsening of pre-existing hypertension, and consider whether discontinuation of EMGALITY is warranted if evaluation fails to establish an alternative etiology or blood pressure is inadequately controlled.

5.3 Raynaud's Phenomenon

Development of Raynaud’s phenomenon and recurrence or worsening of pre-existing Raynaud’s phenomenon have been reported in the postmarketing setting following the use of CGRP antagonists, including EMGALITY. In reported cases with monoclonal antibody CGRP antagonists, symptom onset occurred after a median of 71 days following dosing. Many of the cases reported serious outcomes, including hospitalizations and disability, generally related to debilitating pain. In most reported cases, discontinuation of the CGRP antagonist resulted in resolution of symptoms.

EMGALITY should be discontinued if signs or symptoms of Raynaud’s phenomenon develop, and patients should be evaluated by a healthcare provider if symptoms do not resolve. Patients with a history of Raynaud’s phenomenon should be monitored for, and informed about the possibility of, worsening or recurrence of signs and symptoms.

6 ADVERSE REACTIONS

The following clinically significant adverse reactions are described elsewhere in the labeling:

- Hypersensitivity Reactions [see Contraindications (4) and Warnings and Precautions (5.1)]
- Hypertension [see Warnings and Precautions (5.2)]
- Raynaud's Phenomenon [see Warnings and Precautions (5.3)]

6.1 Clinical Trials Experience

Because clinical trials are conducted under widely varying conditions, adverse reaction rates observed in the clinical trials of a drug cannot be directly compared with rates in clinical trials of another drug and may not reflect the rates observed in clinical practice.

Migraine

The safety of EMGALITY has been evaluated in 2586 patients with migraine who received at least one dose of EMGALITY, representing 1487 patient-years of exposure. Of these, 1920 patients were exposed to EMGALITY once monthly for at least 6 months, and 526 patients were exposed for 12 months.

In placebo-controlled clinical studies (Studies 1, 2, and 3), 705 patients received at least one dose of EMGALITY 120 mg once monthly, and 1451 patients received placebo, during 3 months or 6 months of double-blind treatment [see Clinical Studies (14.1)]. Of the EMGALITY-treated patients, approximately 85% were female, 77% were white, and the mean age was 41 years at study entry.

The most common adverse reaction was injection site reactions. In Studies 1, 2, and 3, 1.8% of patients discontinued double-blind treatment because of adverse events. Table 1 summarizes the adverse reactions that occurred within up to 6 months of treatment in the migraine studies.

Table 1: Adverse Reactions Occurring in Adults with Migraine with an Incidence of at least 2% for EMGALITY and at least 2% Greater than Placebo (up to 6 Months of Treatment) in Studies 1, 2, and 3
Adverse Reaction | EMGALITY 120 mg Monthly (N=705) % | Placebo Monthly (N=1451) %
Injection site reactionsa | 18 | 13
a Injection site reactions include multiple related adverse event terms, such as injection site pain, injection site reaction, injection site erythema, and injection site pruritus.

Episodic Cluster Headache

EMGALITY was studied for up to 2 months in a placebo-controlled trial in patients with episodic cluster headache (Study 4) [see Clinical Studies (14.2)]. A total of 106 patients were studied (49 on EMGALITY and 57 on placebo). Of the EMGALITY-treated patients, approximately 84% were male, 88% were white, and the mean age was 47 years at study entry. Two EMGALITY-treated patients discontinued double-blind treatment because of adverse events.

Overall, the safety profile observed in patients with episodic cluster headache treated with EMGALITY 300 mg monthly is consistent with the safety profile in migraine patients.

6.2 Immunogenicity

As with all therapeutic proteins, there is potential for immunogenicity. The detection of antibody formation is highly dependent on the sensitivity and specificity of the assay. Additionally, the observed incidence of antibody (including neutralizing antibody) positivity in an assay may be influenced by several factors including assay methodology, sample handling, timing of sample collection, concomitant medications, and underlying disease.

For these reasons, comparison of the incidence of antibodies to galcanezumab-gnlm in the studies described below with the incidence of antibodies in other studies or to other products may be misleading.

The immunogenicity of EMGALITY has been evaluated using an in vitro immunoassay for the detection of binding anti-galcanezumab-gnlm antibodies. For patients whose sera tested positive in the screening immunoassay, an in vitro ligand-binding immunoassay was performed to detect neutralizing antibodies.

In controlled studies with EMGALITY up to 6 months (Study 1, Study 2, and Study 3), the incidence of anti-galcanezumab-gnlm antibody development was 4.8% (33/688) in patients receiving EMGALITY once monthly (32 out of 33 of whom had in vitro neutralizing activity). With 12 months of treatment in an open-label study, up to 12.5% (16/128) of EMGALITY-treated patients developed anti-galcanezumab-gnlm antibodies, most of whom tested positive for neutralizing antibodies.

Although anti-galcanezumab-gnlm antibody development was not found to affect the pharmacokinetics, safety or efficacy of EMGALITY in these patients, the available data are too limited to make definitive conclusions.

6.3 Postmarketing Experience

The following adverse reactions have been identified during post-approval use of EMGALITY. Because these reactions are reported voluntarily from a population of uncertain size, it is not always possible to reliably estimate their frequency or establish a causal relationship to EMGALITY exposure.

Immune System Disorders — Anaphylaxis, angioedema [see Contraindications (4) and Warnings and Precautions (5.1)].

Skin and Subcutaneous Tissue Disorders — Rash.

Vascular Disorders — Hypertension [see Warnings and Precautions (5.2)], Raynaud's Phenomenon [see Warnings and Precautions (5.3)]

8 USE IN SPECIFIC POPULATIONS

8.1 Pregnancy

Pregnancy Exposure Registry

There is a pregnancy exposure registry that monitors pregnancy outcomes in women exposed to EMGALITY during pregnancy. Healthcare providers are encouraged to register pregnant patients, or pregnant women may enroll themselves in the registry by calling 1-833-464-4724 or by contacting the company at www.migrainepregnancyregistry.com.

Risk Summary

There are no adequate data on the developmental risk associated with the use of EMGALITY in pregnant women. Administration of galcanezumab-gnlm to rats and rabbits during the period of organogenesis or to rats throughout pregnancy and lactation at plasma exposures greater than that expected clinically did not result in adverse effects on development (see Animal Data).

In the U.S. general population, the estimated background risk of major birth defects and miscarriage in clinically recognized pregnancies is 2% - 4% and 15% - 20%, respectively. The estimated rate of major birth defects (2.2% - 2.9%) and miscarriage (17%) among deliveries to women with migraine are similar to rates reported in women without migraine.

Clinical Considerations

Disease-Associated Maternal and/or Embryo/Fetal Risk

Published data have suggested that women with migraine may be at increased risk of preeclampsia during pregnancy.

Data

Animal Data

When galcanezumab-gnlm was administered to female rats by subcutaneous injection in two studies (0, 30, or 100 mg/kg; 0 or 250 mg/kg) prior to and during mating and continuing throughout organogenesis, no adverse effects on embryofetal development were observed. The highest dose tested (250 mg/kg) was associated with a plasma exposure (Cave, ss) 38 or 18 times that in humans at the recommended human dose (RHD) for migraine (120 mg) or episodic cluster headache (300 mg), respectively. Administration of galcanezumab-gnlm (0, 30, or 100 mg/kg) by subcutaneous injection to pregnant rabbits throughout the period of organogenesis produced no adverse effects on embryofetal development. The higher dose tested was associated with a plasma Cave, ss 64 or 29 times that in humans at 120 mg or 300 mg, respectively.

Administration of galcanezumab-gnlm (0, 30, or 250 mg/kg) by subcutaneous injection to rats throughout pregnancy and lactation produced no adverse effects on pre- and postnatal development. The higher dose tested was associated with a plasma Cave, ss 34 or 16 times that in humans at 120 mg or 300 mg, respectively.

8.2 Lactation

Risk Summary

There are no data on the presence of galcanezumab-gnlm in human milk, the effects on the breastfed infant, or the effects on milk production. The developmental and health benefits of breastfeeding should be considered along with the mother's clinical need for EMGALITY and any potential adverse effects on the breastfed infant from EMGALITY or from the underlying maternal condition.

8.4 Pediatric Use

Safety and effectiveness in pediatric patients have not been established.

8.5 Geriatric Use

Clinical studies of EMGALITY did not include sufficient numbers of patients aged 65 and over to determine whether they respond differently from younger patients.

11 DESCRIPTION

Galcanezumab-gnlm is a humanized IgG4 monoclonal antibody specific for calcitonin-gene related peptide (CGRP) ligand. Galcanezumab-gnlm is produced in Chinese Hamster Ovary (CHO) cells by recombinant DNA technology. Galcanezumab-gnlm is composed of two identical immunoglobulin kappa light chains and two identical immunoglobulin gamma heavy chains and has an overall molecular weight of approximately 147 kDa.

EMGALITY (galcanezumab-gnlm) injection is a sterile, preservative-free, clear to opalescent and colorless to slightly yellow to slightly brown solution, for subcutaneous use. EMGALITY is supplied in a 1 mL single-dose prefilled pen to deliver 120 mg of galcanezumab-gnlm or a 1 mL single-dose prefilled syringe to deliver 100 mg or 120 mg of galcanezumab-gnlm. Each mL of solution contains 100 mg or 120 mg of galcanezumab-gnlm; L-histidine (0.5 mg); L-histidine hydrochloride monohydrate (1.5 mg); Polysorbate 80 (0.5 mg); Sodium Chloride (8.8 mg); Water for Injection, USP. The pH range is 5.3 - 6.3.

12 CLINICAL PHARMACOLOGY

12.1 Mechanism of Action

Galcanezumab-gnlm is a humanized monoclonal antibody that binds to calcitonin gene-related peptide (CGRP) ligand and blocks its binding to the receptor.

12.2 Pharmacodynamics

There are no relevant data on the pharmacodynamic effects of galcanezumab-gnlm.

12.3 Pharmacokinetics

Galcanezumab-gnlm exhibits linear pharmacokinetics and exposure increases proportionally with doses between 1 and 600 mg.

A loading dose of 240 mg achieved the serum galcanezumab-gnlm steady-state concentration after the first dose. A dose of 300 mg monthly would achieve steady-state concentration after the fourth dose. The time to maximum concentration is 5 days, and the elimination half-life is 27 days.

There was no difference in pharmacokinetic parameters between healthy volunteers, patients with episodic or chronic migraine, and patients with episodic cluster headache.

Absorption

Following a subcutaneous dose of galcanezumab-gnlm, the time to maximum concentration was about 5 days.

Injection site location did not significantly influence the absorption of galcanezumab-gnlm.

Distribution

The apparent volume of distribution (V/F) of galcanezumab-gnlm was 7.3 L (34% Inter Individual Variability [IIV]).

Metabolism and Elimination

Galcanezumab-gnlm is expected to be degraded into small peptides and amino acids via catabolic pathways in the same manner as endogenous IgG.

The apparent clearance (CL/F) of galcanezumab-gnlm was 0.008 L/h and the elimination half-life of galcanezumab was approximately 27 days.

Specific Populations

Age, Sex, Weight, Race, Ethnicity

The pharmacokinetics of galcanezumab-gnlm were not affected by age, sex, race, subtypes of migraine spectrum (episodic or chronic migraine), or headache diagnosis (migraine vs. episodic cluster headache) based on a population pharmacokinetics analysis. Body weight has no clinically relevant effect on the pharmacokinetics of galcanezumab-gnlm.

Patients with Renal or Hepatic Impairment

Renal and hepatic impairment are not expected to affect the pharmacokinetics of galcanezumab-gnlm. Population pharmacokinetic analysis of integrated data from the galcanezumab-gnlm clinical studies revealed that creatinine clearance did not affect the pharmacokinetics of galcanezumab-gnlm in patients with mild or moderate renal impairment. Patients with severe renal impairment (creatinine clearance <30 mL/min) have not been studied. Based on a population PK analysis, bilirubin concentration did not significantly influence the CL/F of galcanezumab-gnlm.

No dedicated clinical studies were conducted to evaluate the effect of hepatic impairment or renal impairment on the pharmacokinetics of galcanezumab-gnlm.

Drug Interaction Studies

P450 Enzymes

Galcanezumab-gnlm is not metabolized by cytochrome P450 enzymes; therefore, interactions with concomitant medications that are substrates, inducers, or inhibitors of cytochrome P450 enzymes are unlikely.

13 NONCLINICAL TOXICOLOGY

13.1 Carcinogenesis, Mutagenesis, Impairment of Fertility

Carcinogenesis

The carcinogenic potential of galcanezumab-gnlm has not been assessed.

Mutagenesis

Genetic toxicology studies of galcanezumab-gnlm have not been conducted.

Impairment of Fertility

When galcanezumab-gnlm (0, 30, or 250 mg/kg) was administered to male rats by subcutaneous injection prior to and during mating, no adverse effects on fertility was observed. The higher dose tested was associated with a plasma exposure (Cave, ss) 8 or 4 times that in humans at the recommended human dose (RHD) for migraine (120 mg) or episodic cluster headache (300 mg), respectively. When galcanezumab-gnlm was administered to female rats by subcutaneous injection in two studies (0, 30, or 100 mg/kg; 0 or 250 mg/kg) prior to and during mating and continuing throughout organogenesis, no adverse effects on fertility were observed. The highest dose tested (250 mg/kg) was associated with a plasma Cave, ss 38 or 18 times that in humans at 120 mg or 300 mg, respectively.

14 CLINICAL STUDIES

14.1 Migraine

The efficacy of EMGALITY was evaluated as a preventive treatment of episodic or chronic migraine in three multicenter, randomized, double-blind, placebo-controlled studies: two 6-month studies in patients with episodic migraine (Studies 1 and 2) and one 3-month study in patients with chronic migraine (Study 3).

Episodic Migraine

Study 1 (NCT02614183) and Study 2 (NCT02614196) included adults with a history of episodic migraine (4 to 14 migraine days per month). All patients were randomized in a 1:1:2 ratio to receive once-monthly subcutaneous injections of EMGALITY 120 mg, EMGALITY 240 mg, or placebo. All patients in the 120 mg EMGALITY group received an initial 240 mg loading dose. Patients were allowed to use acute headache treatments, including migraine-specific medications (i.e., triptans, ergotamine derivatives), NSAIDs, and acetaminophen during the study.

The studies excluded patients on any other migraine preventive treatment, patients with medication overuse headache, patients with ECG abnormalities compatible with an acute cardiovascular event and patients with a history of stroke, myocardial infarction, unstable angina, percutaneous coronary intervention, coronary artery bypass grafting, deep vein thrombosis, or pulmonary embolism within 6 months of screening.

The primary efficacy endpoint for Studies 1 and 2 was the mean change from baseline in the number of monthly migraine headache days over the 6-month treatment period. Key secondary endpoints included response rates (the mean percentages of patients reaching at least 50%, 75%, and 100% reduction from baseline in the number of monthly migraine headache days over the 6-month treatment period), the mean change from baseline in the number of monthly migraine headache days with use of any acute headache medication during the 6-month treatment period, and the impact of migraine on daily activities, as assessed by the mean change from baseline in the average Migraine-Specific Quality of Life Questionnaire version 2.1 (MSQ v2.1) Role Function-Restrictive domain score during the last 3 months of treatment (Months 4 to 6). Scores are scaled from 0 to 100, with higher scores indicating less impact of migraine on daily activities.

In Study 1, a total of 858 patients (718 females, 140 males) ranging in age from 18 to 65 years, were randomized. A total of 703 patients completed the 6-month double-blind phase. In Study 2, a total of 915 patients (781 female, 134 male) ranging in age from 18 to 65 years, were randomized. A total of 785 patients completed the 6-month double-blind phase. In Study 1 and Study 2, the mean migraine frequency at baseline was approximately 9 migraine days per month, and was similar across treatment groups.

EMGALITY 120 mg demonstrated statistically significant improvements for efficacy endpoints compared to placebo over the 6-month period, as summarized in Table 2. EMGALITY treatment with the 240 mg once-monthly dose showed no additional benefit over the EMGALITY 120 mg once-monthly dose.

Table 2: Efficacy Endpoints in Studies 1 and 2
 | Study 1 |  | Study 2
 | EMGALITY 120 mg N = 210 | Placebo N = 425 | EMGALITY 120 mg N = 226 | Placebo N = 450
Monthly Migraine Headache Days (over Months 1 to 6)
Baseline migraine headache days | 9.2 | 9.1 | 9.1 | 9.2
Mean change from baseline | -4.7 | -2.8 | -4.3 | -2.3
Difference from placeboa | -1.9 |  | -2.0
≥50% Migraine Headache Days Responders (over Months 1 to 6)
% Respondersa | 62% | 39% | 59% | 36%
≥75% Migraine Headache Days Responders (over Months 1 to 6)
% Respondersa | 39% | 19% | 34% | 18%
100% Migraine Headache Days Responders (over Months 1 to 6)
% Respondersa | 16% | 6% | 12% | 6%
Monthly Migraine Headache Days that Acute Medication was Taken (over Months 1 to 6)
Mean change from baseline (days)a | -4.0 | -2.2 | -3.7 | -1.9
MSQ Role Function-Restrictive Domain Score (over Months 4 to 6)
Baseline | 51.4 | 52.9 | 52.5 | 51.4
Mean change from baselineb | 32.4 | 24.7 | 28.5 | 19.7
Difference from placeboa | 7.7 |  | 8.8
a p<0.001
b N = 189 for EMGALITY 120 mg and N = 377 for placebo in Study 1; N = 213 for EMGALITY 120 mg and N = 396 for placebo in Study 2.

Figure 1: Change from Baseline in Monthly Migraine Headache Days in Study 1 a

a Least-square means and 95% confidence intervals are presented.

Figure 2: Change from Baseline in Monthly Migraine Headache Days in Study 2 a

a Least-square means and 95% confidence intervals are presented.

Figure 3 shows the distribution of change from baseline in the mean number of monthly migraine headache days in bins of 2 days, by treatment group, in Study 1. A treatment benefit over placebo for EMGALITY is seen across a range of changes from baseline in monthly migraine headache days.

Figure 3: Distribution of Change from Baseline in Mean Monthly Migraine Headache Days over Months 1 to 6 by Treatment Group in Study 1

Figure 4 shows the distribution of change from baseline in the mean number of monthly migraine headache days in bins of 2 days, by treatment group, in Study 2. A treatment benefit over placebo for EMGALITY is seen across a range of changes from baseline in monthly migraine headache days.

Figure 4: Distribution of Change from Baseline in Mean Monthly Migraine Headache Days over Months 1 to 6 by Treatment Group in Study 2

Chronic Migraine

Study 3 (NCT02614261) included adults with a history of chronic migraine (≥15 headache days per month with ≥8 migraine days per month). All patients were randomized in a 1:1:2 ratio to receive once-monthly subcutaneous injections of EMGALITY 120 mg, EMGALITY 240 mg, or placebo over a 3-month treatment period. All patients in the 120 mg EMGALITY group received an initial 240 mg loading dose.

Patients were allowed to use acute headache treatments including migraine-specific medications (i.e., triptans, ergotamine derivatives), NSAIDs, and acetaminophen. A subset of patients (15%) was allowed to use one concomitant migraine preventive medication. Patients with medication overuse headache were allowed to enroll.

The study excluded patients with ECG abnormalities compatible with an acute cardiovascular event, and patients with a history of stroke, myocardial infarction, unstable angina, percutaneous coronary intervention, coronary artery bypass grafting, deep vein thrombosis, or pulmonary embolism within 6 months of screening.

The primary endpoint was the mean change from baseline in the number of monthly migraine headache days over the 3-month treatment period. The secondary endpoints were response rates (the mean percentages of patients reaching at least 50%, 75% and 100% reduction from baseline in the number of monthly migraine headache days over the 3-month treatment period), the mean change from baseline in the number of monthly migraine headache days with use of any acute headache medication during the 3-month treatment period, and the impact of migraine on daily activities as assessed by the mean change from baseline in the MSQ v2.1 Role Function-Restrictive domain score at Month 3. Scores are scaled from 0 to 100, with higher scores indicating less impact of migraine on daily activities.

In Study 3, a total of 1113 patients (946 female, 167 male) ranging in age from 18 to 65 years, were randomized. A total of 1037 patients completed the 3-month double-blind phase. The mean number of monthly migraine headache days at baseline was approximately 19.

EMGALITY 120 mg demonstrated statistically significant improvement for the mean change from baseline in the number of monthly migraine headache days over the 3-month treatment period, and in the mean percentage of patients reaching at least 50% reduction from baseline in the number of monthly migraine headache days over the 3-month treatment period, as summarized in Table 3. EMGALITY treatment with the 240 mg once-monthly dose showed no additional benefit over the EMGALITY 120 mg once-monthly dose.

Table 3: Efficacy Endpoints in Study 3
 | EMGALITY 120 mg N = 273 | Placebo N =538
Monthly Migraine Headache Days (over Months 1 to 3)
Baseline migraine headache days | 19.4 | 19.6
Mean change from baseline | -4.8 | -2.7
Difference from placeboa | -2.1
≥50% Migraine Headache Days Responders (over Months 1 to 3)
% Respondersa | 28% | 15%
a p<0.001

Study 3 utilized a sequential testing procedure to control the Type-I error rate for the multiple secondary endpoints. Once a secondary endpoint failed to reach the required level for statistical significance, formal hypothesis testing was terminated for subsequent endpoints, and p-values were considered nominal only. In Study 3, EMGALITY 120 mg was not significantly better than placebo for the proportion of patients with ≥75% or 100% reduction in migraine headache days. Patients treated with EMGALITY 120 mg showed a nominally greater reduction in the number of monthly migraine headache days that acute medication was taken (-4.7 for EMGALITY 120 mg vs. -2.2 for placebo; nominal p-value <0.001), and the mean change from baseline in the MSQ Role Function-Restrictive Domain score at Month 3 was nominally greater in patients treated with EMGALITY 120 mg than in patients on placebo (21.8 for EMGALITY 120 mg vs. 16.8 for placebo; nominal p-value <0.001).

Figure 5: Change from Baseline in Monthly Migraine Headache Days in Study 3 a

a Least-square means and 95% confidence intervals are presented.

Figure 6 shows the distribution of change from baseline in the mean number of monthly migraine headache days for the 3-month study period in bins of 3 days by treatment group. A treatment benefit over placebo for EMGALITY is seen across a range of changes from baseline in monthly migraine headache days.

Figure 6: Distribution of Change from Baseline in Mean Monthly Migraine Headache Days over Months 1 to 3 by Treatment Group in Study 3

14.2 Episodic Cluster Headache

The efficacy of EMGALITY was evaluated for the treatment of episodic cluster headache in a randomized, 8-week, double-blind, placebo-controlled study (Study 4).

Study 4 (NCT02397473) included adults who met the International Classification of Headache Disorders 3rd edition (beta version) diagnostic criteria for episodic cluster headache and had a maximum of 8 attacks per day, a minimum of one attack every other day, and at least 4 attacks during the prospective 7-day baseline period. All patients were randomized in a 1:1 ratio to receive once-monthly subcutaneous injections of EMGALITY 300 mg or placebo. Patients were allowed to use certain specified acute/abortive cluster headache treatments, including triptans, oxygen, acetaminophen, and NSAIDs during the study.

The study excluded patients on other treatments intended to reduce the frequency of cluster headache attacks; patients with medication overuse headache; patients with ECG abnormalities compatible with an acute cardiovascular event or conduction delay; and patients with a history of myocardial infarction, unstable angina, percutaneous coronary intervention, coronary artery bypass grafting, deep vein thrombosis, or pulmonary embolism within 6 months of screening. In addition, patients with any history of stroke, intracranial or carotid aneurysm, intracranial hemorrhage, or vasospastic angina; clinical evidence of peripheral vascular disease; or diagnosis of Raynaud’s disease were excluded.

The primary efficacy endpoint for Study 4 was the mean change from baseline in weekly cluster headache attack frequency across Weeks 1 to 3. A secondary endpoint was the percentage of patients who achieved a response (defined as a reduction from baseline of 50% or greater in the weekly cluster headache attack frequency) at Week 3.

In Study 4, a total of 106 patients (88 males, 18 females) ranging in age from 19 to 65 years were randomized and treated. A total of 90 patients completed the 8-week double-blind phase. In the prospective baseline phase, the mean number of weekly cluster headache attacks was 17.5, and was similar across treatment groups.

EMGALITY 300 mg demonstrated statistically significant improvements for efficacy endpoints compared to placebo, as summarized in Table 4.

Table 4: Efficacy Endpoints in Study 4
 | EMGALITY 300 mg N = 49 | Placebo N = 57
Mean Reduction in Weekly Cluster Headache Attack Frequency (over Weeks 1 to 3)
Prospective Baseline Cluster Headache Attack Frequency | 17.8 | 17.3
Mean change from baseline | -8.7 | -5.2
Difference from placebo | -3.5
p-value | 0.036
≥50% Weekly Cluster Headache Attack Frequency Responders (at Week 3)
% Responders | 71.4% | 52.6%
Difference from placebo | 18.8%
p-value | 0.046

Figure 7: Mean Change in Weekly Cluster Headache Attack Frequency over Weeks 1 to 3 in Study 4a

a Abbreviations: BL = baseline; LS = least square; SE = standard error.

Figure 8 shows the distribution of the average percent change from baseline in weekly cluster headache attack frequency across Weeks 1 to 3 in bins of 25%, by treatment group, in Study 4.

Figure 8: Distribution of the Average Percent Change from Baseline in Weekly Cluster Headache Attack Frequency over Weeks 1 to 3 in Study 4 a

a N = number of intent to treat patients with non-missing average percentage change from baseline in weekly cluster headache attack frequency over weeks 1 to 3.

16 HOW SUPPLIED/STORAGE AND HANDLING

16.1 How Supplied

EMGALITY (galcanezumab-gnlm) injection is a sterile, preservative-free, clear to opalescent, colorless to slightly yellow to slightly brown solution for subcutaneous administration.

EMGALITY is not made with natural rubber latex.

EMGALITY is supplied as follows:

 | Pack Size | NDC
Prefilled pen
120 mg/mL single-dose | Carton of 1 | 0002-1436-11
120 mg/mL single-dose | Carton of 2 | 0002-1436-27
Prefilled syringe
100 mg/mL single-dose | Carton of 3 | 0002-3115-09
120 mg/mL single-dose | Carton of 1 | 0002-2377-11
120 mg/mL single-dose | Carton of 2 | 0002-2377-27

16.2 Storage and Handling

- Store refrigerated at 2°C to 8°C (36°F to 46°F) in the original carton to protect EMGALITY from light until use.
- Do not freeze.
- Do not shake.
- EMGALITY may be stored out of refrigeration in the original carton at temperatures up to 30°C (86°F) for up to 7 days. Once stored out of refrigeration, do not place back in the refrigerator.
- If these conditions are exceeded, EMGALITY must be discarded.
- Discard the EMGALITY single-dose prefilled pen or syringe after use in a puncture-resistant container.

17 PATIENT COUNSELING INFORMATION

Advise the patient to read the FDA-approved patient labeling (Patient Information and Instructions for Use).

Instructions on Self-Administration: Provide guidance to patients and/or caregivers on proper subcutaneous injection technique, including aseptic technique, and how to use the prefilled pen or prefilled syringe correctly [see Instructions for Use]. Instruct patients and/or caregivers to read and follow the Instructions for Use each time they use EMGALITY.

Hypersensitivity Reactions:

Inform patients about the signs and symptoms of hypersensitivity reactions and that these reactions can occur with EMGALITY. Advise patients to seek immediate medical attention if they experience any symptoms of serious or severe hypersensitivity reactions [see Warnings and Precautions (5.1)].

Hypertension:

Inform patients that hypertension can develop or pre-existing hypertension can worsen with EMGALITY, and that they should contact their healthcare provider if they experience elevation in their blood pressure [see Warnings and Precautions (5.2)].

Raynaud's Phenomenon:

Inform patients that Raynaud's phenomenon can develop or worsen with EMGALITY. Advise patients to discontinue EMGALITY and contact their healthcare provider if they experience signs or symptoms of Raynaud's phenomenon [see Warnings and Precautions (5.3)].

Pregnancy Exposure Registry: Advise patients that there is a pregnancy exposure registry that monitors pregnancy outcomes in women exposed to EMGALITY during pregnancy [see Use in Specific Populations (8.1)].

For more information go to www.emgality.com or call 1-800-LillyRx (1-800-545-5979).

Literature revised: 10/2025

Eli Lilly and Company, Indianapolis, IN 46285, USA

US License Number 1891

Copyright © 2018, 2025, Eli Lilly and Company. All rights reserved.

Pat.: www.lilly.com/patents

EMG-0009-USPI-20251021

PATIENT INFORMATION
EMGALITY® (em-GAL-it-ē)
(galcanezumab-gnlm)
injection, for subcutaneous use

What is EMGALITY?
EMGALITY is a prescription medicine used in adults for the:

- preventive treatment of migraine.
- treatment of episodic cluster headache.

It is not known if EMGALITY is safe and effective in children.

Who should not use EMGALITY?
Do not use EMGALITY if you are allergic to galcanezumab-gnlm or any of the ingredients in EMGALITY. See the end of this Patient Information for a complete list of ingredients in EMGALITY.

Before you use EMGALITY, tell your healthcare provider if you:

- have high blood pressure.
- have circulation problems in your fingers and toes.
- are pregnant or plan to become pregnant. It is not known if EMGALITY will harm your unborn baby.
  - Pregnancy Registry: There is a pregnancy registry for women who take EMGALITY. The purpose of this registry is to collect information about the health of you and your baby. You may enroll yourself by calling 1-833-464-4724 or by visiting www.migrainepregnancyregistry.com. Or you may talk to your healthcare provider about how you can take part in this registry.
- are breastfeeding or plan to breastfeed. It is not known if EMGALITY passes into your breast milk. Talk to your healthcare provider about the best way to feed your baby while using EMGALITY.

Tell your healthcare provider about all the medicines you take, including prescription and over-the-counter medicines, vitamins, and herbal supplements. Know the medicines you take. Keep a list of your medicines with you to show your healthcare provider and pharmacist when you get a new medicine.

How should I use EMGALITY?

- See the Instructions for Use that come with EMGALITY prefilled pen or prefilled syringe about how to use EMGALITY the right way.
- Use EMGALITY exactly as your healthcare provider tells you to.
- EMGALITY is given by injection under the skin (subcutaneous injection).
- Inject EMGALITY in your stomach area (abdomen), thigh, back of the upper arm, or buttocks.
- Your healthcare provider should show you or a caregiver how to prepare and inject EMGALITY the right way before you start to use it.
- EMGALITY comes in 2 different types of devices:
  - a single-dose (1 time) prefilled pen
  - a single-dose (1 time) prefilled syringe
  Your healthcare provider will prescribe the type that is best for you.
- If you have questions about injecting the medicine, talk to your pharmacist or healthcare provider.
- If you are using the EMGALITY 120 mg prefilled pen or prefilled syringe for migraine:
  - Inject EMGALITY 1 time each month.
  - For the first dose (loading dose), you will get 2 separate injections one time, right after each other. You will need 2 prefilled pens or 2 prefilled syringes for your first dose (1-time loading dose).
  - For your regular monthly dose, you will get 1 injection. You will need 1 prefilled pen or 1 prefilled syringe for your regular monthly dose.
  - If you miss a dose of EMGALITY, inject the missed dose as soon as possible. Then inject EMGALITY 1 month from the date of your last dose to get back on a monthly dosing schedule. If you have questions about your schedule, ask your healthcare provider.
- If you are using the EMGALITY 100 mg prefilled syringe for episodic cluster headache:
  - You will get 3 separate injections, right after each other, using 3 prefilled syringes for each of your doses.
  - Use EMGALITY at the start of a cluster period and then every month until the end of the cluster period.
- If you miss a dose of EMGALITY, inject the missed dose as soon as possible. Then, if the cluster headache period has not yet ended, inject EMGALITY 1 month after your last dose to get back on a monthly dosing schedule. If you have questions about when you should use EMGALITY, ask your healthcare provider.

What are the possible side effects of EMGALITY?
EMGALITY may cause serious side effects, including:

- Allergic reactions. Allergic reactions, including itching, rash, hives, and trouble breathing, can happen after receiving EMGALITY. This can happen days after using EMGALITY. Call your healthcare provider or get emergency medical help right away if you have any of the following symptoms, which may be part of an allergic reaction:
  - swelling of the face, mouth, tongue, or throat
  - trouble breathing
- High blood pressure. High blood pressure or worsening of high blood pressure can happen after receiving EMGALITY. Contact your healthcare provider if you have an increase in blood pressure.
- Raynaud’s phenomenon. A type of circulation problem can worsen or happen after receiving EMGALITY. Raynaud’s phenomenon can lead to your fingers or toes feeling numb, cool, or painful, or changing color from pale, to blue, to red. Contact your healthcare provider if these symptoms occur.

The most common side effects of EMGALITY include:

- injection site reactions

Tell your healthcare provider if you have any side effect that bothers you or that does not go away.
These are not all of the possible side effects of EMGALITY. For more information, ask your healthcare provider or pharmacist.
Call your healthcare provider for medical advice about side effects. You may report side effects to FDA at 1-800-FDA-1088.

How should I store EMGALITY?

- Store EMGALITY in the refrigerator between 36°F to 46°F (2°C to 8°C).
- EMGALITY may be stored out of the refrigerator in the original carton at temperatures up to 86°F (30°C) for up to 7 days. After storing out of the refrigerator, do not place EMGALITY back in the refrigerator.
- Do not freeze EMGALITY.
- Keep EMGALITY in the carton it comes in to protect it from light until time of use.
- Do not shake EMGALITY.
- Throw away EMGALITY if any of the above conditions are not followed.

Keep EMGALITY and all medicines out of the reach of children.

General information about the safe and effective use of EMGALITY.
Medicines are sometimes prescribed for purposes other than those listed in the Patient Information. Do not use EMGALITY for a condition for which it was not prescribed. Do not give EMGALITY to other people, even if they have the same symptoms you have. It may harm them.
You can ask your pharmacist or healthcare provider for information about EMGALITY that is written for health professionals.

What are the ingredients in EMGALITY?
Active ingredient: galcanezumab-gnlm
Inactive ingredients: L-histidine, L-histidine hydrochloride monohydrate, Polysorbate 80, Sodium Chloride, and Water for Injection, USP.
EMGALITY prefilled pen and prefilled syringes are not made with natural rubber latex.
EMGALITY® is a registered trademark of Eli Lilly and Company.
Eli Lilly and Company Indianapolis, IN 46285, USA
US License Number 1891
Copyright © 2018, 2025, Eli Lilly and Company. All rights reserved.
EMG-0007-PPI-20251021
For more information, call 1-800-LillyRx (1-800-545-5979) or go to www.emgality.com.

This Patient Information has been approved by the U.S. Food and Drug Administration

Revised: 10/2025

INSTRUCTIONS FOR USE

EMGALITY® [em-GAL-it-ē]

(galcanezumab-gnlm)

injection, for subcutaneous use

Prefilled Pen

This Instructions for Use contains information on how to inject EMGALITY

This Instructions for Use is for patients with migraine.

For subcutaneous injection only.

Important Information You Need to Know Before Injecting EMGALITY

- Your healthcare provider or nurse should show you how to prepare and inject EMGALITY using the Pen. Do not inject yourself or someone else until you have been shown how to inject EMGALITY.

- Keep this Instructions for Use and refer to it as needed.

- Each EMGALITY Pen is for one-time use only. Do not share or reuse your EMGALITY Pen. You may give or get an infection.

- The Pen contains glass parts. Handle it carefully. If you drop it on a hard surface, do not use it. Use a new Pen for your injection.

- Your healthcare provider may help you decide where on your body to inject your dose. You can also read the “Choose your injection site” section of these instructions to help you choose which area can work best for you.

- If you have vision or hearing problems, do not use EMGALITY Pen without help from a caregiver.

- See “Storing EMGALITY” for important storage information.

INSTRUCTIONS FOR USE

Before you use the EMGALITY Pen, read and carefully follow all the step-by-step instructions.

Parts of the EMGALITY Pen

Step 1 Preparing to Inject EMGALITY

Step 1a Take the Pen from the refrigerator

Check your prescription.

- EMGALITY comes as a single-dose prefilled Pen.
- You will need 2 Pens for your first dose (1-time loading dose). You will need 1 Pen for your monthly dose.

Put the original package with any unused Pens back in the refrigerator.

Leave the base cap on until you are ready to inject.

Leave the Pen at room temperature for 30 minutes before injecting.

Do not microwave the Pen, run hot water over it, or leave it in direct sunlight.

Do not shake.

Step 1b Gather Supplies

For each injection you will need:

- 1 alcohol wipe
- 1 cotton ball or piece of gauze
- 1 sharps disposal container. See “After You Inject Your Medicine.”

Step 1c Inspect the Pen and the medicine

Make sure you have the right medicine. The medicine inside should be clear. Its color may be colorless to slightly yellow to slightly brown.

Do not use the Pen, and throw away (dispose of) as directed by your healthcare provider or pharmacist if:

- it looks damaged
- the medicine is cloudy, is discolored, or has small particles
- the Expiration Date (Exp.) printed on the label has passed (see Figure A)
- the medicine is frozen

Figure A

Step 1d Prepare for injection

Wash your hands with soap and water before you inject your EMGALITY. Make sure a sharps disposal container is close by.

Step 1e Choose your injection site

Your healthcare provider can help you choose the injection site that is best for you.

Figure B

- You may inject the medicine into your stomach area (abdomen). Do not inject within 2 inches of the belly button (navel) (see Figure B).

- You may inject the medicine into the front of your thighs. This area should be at least 2 inches above the knee and 2 inches below the groin.

- Another person may give you the injection in the back of your upper arm, or buttocks (see Figure B).

- Do not inject in the exact same spot. For example, if you are giving 2 injections for your first dose (1-time loading dose) and want to use the same body site for the two separate injections, choose a different injection spot. If your first injection was in your abdomen, your next injection could be in another area of your abdomen.

- Do not inject into areas where the skin is tender, bruised, red, or hard.

- Clean your injection site with an alcohol wipe. Let the injection site dry before you inject.

Step 2 Injecting EMGALITY

Step 2a Uncap the Pen

Figure C

Make sure the Pen is locked. Leave the base cap on until you are ready to inject.

- Twist off the base cap (see Figure C) and throw it away in your household trash.

- Do not put the base cap back on – this could damage the needle.

- Do not touch the needle.

Step 2b Place and Unlock

Figure D

- Place and hold the clear base flat and firmly against your skin (see Figure D).

Turn the lock ring to the unlock position.

Step 2c Press and Hold for 10 Seconds

Figure E

- Press and hold the teal injection button; you will hear a loud click (see Figure E).

- Keep holding the clear base firmly against your skin. You will hear a second click in about 10 seconds after the first one. This second click tells you that your injection is complete.

- Remove the Pen from your skin.
- If you have bleeding at the injection site, press a cotton ball or gauze over the injection site. Do not rub the injection site.

Figure F

Step 3 Disposing of EMGALITY

Step 3a Throw away the used Pen

- Put the used EMGALITY Pen in an FDA-cleared sharps disposal container right away after use (see Figure G). Do not throw away (dispose of) the EMGALITY Pen in your household trash.

Figure G

- If you do not have an FDA-cleared sharps disposal container, you may use a household container that is:
  - made of a heavy-duty plastic,
  - can be closed with a tight-fitting, puncture-resistant lid, without sharps being able to come out,
  - upright and stable during use,
  - leak-resistant, and
  - properly labeled to warn of hazardous waste inside the container.
- When your sharps disposal container is almost full, you will need to follow your community guidelines for the right way to dispose of your sharps disposal container. There may be state or local laws about how you should throw away needles and syringes. For more information about safe sharps disposal, and for specific information about sharps disposal in the state you live in, go to the FDA's website at: http://www.fda.gov/safesharpsdisposal.
- Do not recycle your used sharps disposal container.

Commonly Asked Questions
Q. | What if I see bubbles in the Pen?
A. | It is normal to have air bubbles in the Pen. EMGALITY is injected under your skin (subcutaneous injection), so these air bubbles will not harm you.
Q. | What if there is a drop of liquid on the tip of the needle when I remove the base cap?
A. | It is okay to see a drop of liquid on the tip of the needle.
Q. | What if I unlocked the Pen and pressed the teal injection button before I twisted off the base cap?
A. | Do not remove the base cap. Dispose of the Pen and get a new one.
Q. | Do I need to hold the injection button down until the injection is complete?
A. | This is not necessary, but it may help you keep the Pen steady and firm against your skin.
Q. | What if the needle did not retract after my injection?
A. | Do not touch the needle or replace the base cap. Store in a safe place to avoid an accidental needlestick and contact 1-800-545-5979 for instructions on how to return the Pen.
Q. | What if there is a drop of liquid or blood on my skin after my injection?
A. | This is normal. Press a cotton ball or gauze over the injection site. Do not rub the injection site.
Q. | What if I heard more than 2 clicks during my injection – 2 loud clicks and a soft one. Did I get my complete injection?
A. | Some patients may hear a soft click right before the second loud click. That is the normal operation of the Pen. Do not remove the Pen from your skin until you hear the second loud click.
Q. | How can I tell if my injection is complete?
A. | After you press the teal injection button, you will hear 2 loud clicks. The second click tells you that your injection is complete. You will also see the gray plunger at the top of the clear base.
If you have more questions about how to use the EMGALITY Pen:
- Call your healthcare provider - Call 1-800-LillyRx (1-800-545-5979) - Visit www.emgality.com

Storing EMGALITY

- Store your Pen in the refrigerator between 36ºF to 46ºF (2ºC to 8ºC).

- Your Pen may be stored out of the refrigerator in the original carton at temperatures up to 86°F (30°C) for up to 7 days. After storing out of the refrigerator, do not place EMGALITY back in the refrigerator.

- Do not freeze your Pen.

- Keep your Pen in the carton it comes in to protect it from light until time of use.

- Do not shake your Pen.

- Throw away your Pen if any of the above conditions are not followed.

- Keep your Pen and all medicines out of the reach of children.

Read the full Prescribing Information and Patient Information for EMGALITY inside this box to learn more about your medicine.

Eli Lilly and Company
Indianapolis, IN 46285, USA

US License Number 1891

EMGALITY® is a registered trademark of Eli Lilly and Company.

Copyright © 2018, 2025, Eli Lilly and Company. All rights reserved.

The Pen meets the current dose accuracy and functional requirements of ISO 11608-1 and 11608-5.
This Instructions for Use has been approved by the U.S. Food and Drug Administration.
Revised: 11/2025

EMG-0006-AI-120MG-IFU-20251119

INSTRUCTIONS FOR USE

EMGALITY® [em-GAL-it-ē]

(galcanezumab-gnlm)

injection, for subcutaneous use

Prefilled Syringe

This Instructions for Use contains information on how to inject EMGALITY

This Instructions for Use is for patients with migraine.

- If you are using EMGALITY for episodic cluster headache, there is a different Instructions for Use because the dose and number of syringes needed is different.

For subcutaneous injection only.

Important Information You Need to Know Before Injecting EMGALITY

- Your healthcare provider or nurse should show you how to prepare and inject EMGALITY using the prefilled syringe. Do not inject yourself or someone else until you have been shown how to inject EMGALITY.

- Keep this Instructions for Use and refer to it as needed.

- Each EMGALITY prefilled syringe is for one-time use only. Do not share or reuse your EMGALITY prefilled syringe. You may give or get an infection.

- Your healthcare provider may help you decide where on your body to inject your dose. You can also read the “Choose your injection site” section of these instructions to help you choose which area can work best for you.

- If you have vision problems, do not use EMGALITY prefilled syringe without help from a caregiver.

- See “Storing EMGALITY” for important storage information.

INSTRUCTIONS FOR USE

Before you use the EMGALITY prefilled syringe, read and carefully follow all the step-by-step instructions.

Parts of the EMGALITY Prefilled Syringe

Step 1 Preparing to Inject EMGALITY

Step 1a Take the Prefilled Syringe from the refrigerator

Check your prescription.

- EMGALITY comes as a single-dose prefilled syringe.
- You will need 2 prefilled syringes for your first dose (1-time loading dose). You will need 1 prefilled syringe for your monthly dose.

Put the original package with any unused syringes back in the refrigerator.

Leave the needle cap on until you are ready to inject.

Leave the prefilled syringe at room temperature for 30 minutes before injecting.

Do not microwave the prefilled syringe, run hot water over it, or leave it in direct sunlight.

Do not shake.

Step 1b Gather Supplies

For each injection you will need:

- 1 alcohol wipe
- 1 cotton ball or piece of gauze
- 1 sharps disposal container. See “After You Inject Your Medicine.”

Step 1c Inspect the Prefilled Syringe and the medicine

Make sure you have the right medicine. The medicine inside should be clear. Its color may be colorless to slightly yellow to slightly brown.

Do not use the prefilled syringe, and throw away (dispose of) as directed by your healthcare provider or pharmacist if:

- it looks damaged
- the medicine is cloudy, is discolored, or has small particles
- the Expiration Date (Exp.) printed on the label has passed (see Figure A)
- the medicine is frozen

Figure A

Step 1d Prepare for injection

Wash your hands with soap and water before you inject your EMGALITY. Make sure a sharps disposal container is close by.

Step 1e Choose your injection site

Your healthcare provider can help you choose the injection site that is best for you.

Figure B

- You may inject the medicine into your stomach area (abdomen). Do not inject within 2 inches of the belly button (navel) (see Figure B).

- You may inject the medicine into the front of your thighs. This area should be at least 2 inches above the knee and 2 inches below the groin.

- Another person may give you the injection in the back of your upper arm, or buttocks (see Figure B).

- Do not inject in the exact same spot. For example, if you are giving 2 injections for your first dose (1-time loading dose) and want to use the same body site for the two separate injections, choose a different injection spot. If your first injection was in your abdomen, your next injection could be in another area of your abdomen.

- Do not inject into areas where the skin is tender, bruised, red, or hard.

- Clean your injection site with an alcohol wipe. Let the injection site dry before you inject.

Step 2 Injecting EMGALITY

Step 2a Uncap

Figure C

- Leave the needle cap on until you are ready to inject.

- Pull the needle cap off (see Figure C) and throw it away in your household trash.

- Do not put the needle cap back on. You could damage the needle or stick yourself by accident.

- Do not touch the needle.

Step 2b Insert

Figure D

- Gently pinch and hold a fold of skin where you will inject (see Figure D).

- Insert the needle at a 45-degree angle.

Step 2c Inject

Figure E

- Slowly push on the thumb pad to push the plunger all the way in until all the medicine is injected (see Figure E).

- The gray syringe plunger should be pushed all the way to the needle end of the syringe (see Figure F).

- You should see the teal plunger rod show through the syringe body when the injection is complete as shown (see Figure F).
- Remove the needle from your skin and gently let go of your skin.
- If you have bleeding at the injection site, press a cotton ball or gauze over the injection site. Do not rub the injection site.
- Do not put the needle cap back on the prefilled syringe.

Figure F

Step 3 Disposing of EMGALITY

Step 3a Throw away the used prefilled syringe

- Put the used EMGALITY prefilled syringe in an FDA-cleared sharps disposal container right away after use (see Figure G). Do not throw away (dispose of) the EMGALITY prefilled syringe in your household trash.

Figure G

- If you do not have an FDA-cleared sharps disposal container, you may use a household container that is:
  - made of a heavy-duty plastic,
  - can be closed with a tight-fitting, puncture-resistant lid, without sharps being able to come out,
  - upright and stable during use,
  - leak-resistant, and
  - properly labeled to warn of hazardous waste inside the container.
- When your sharps disposal container is almost full, you will need to follow your community guidelines for the right way to dispose of your sharps disposal container. There may be state or local laws about how you should throw away needles and syringes. For more information about safe sharps disposal, and for specific information about sharps disposal in the state you live in, go to the FDA's website at: http://www.fda.gov/safesharpsdisposal.
- Do not recycle your used sharps disposal container.

Commonly Asked Questions
Q. | What if I see air bubbles in my EMGALITY prefilled syringe?
A. | It is normal to have air bubbles in the prefilled syringe. EMGALITY is injected under your skin (subcutaneous injection), so these air bubbles will not harm you.
Q. | What if there is a drop of liquid on the tip of the needle when I remove the needle cap?
A. | It is okay to see a drop of liquid on the tip of the needle.
Q. | What if I cannot push in the plunger?
A. | If the plunger is stuck or damaged:
 | - Do not continue to use the syringe
 | - Remove the needle from your skin
 | - Dispose of the syringe and get a new one
Q. | What if there is a drop of liquid or blood on my skin after my injection?
A. | This is normal. Press a cotton ball or gauze over the injection site. Do not rub the injection site.
Q. | How can I tell if my injection is complete?
A. | When your injection is complete:
 | - The teal plunger rod should show through the body of the syringe.
 | - The gray syringe plunger should be pushed all the way to the needle end of the syringe.
If you have more questions about how to use the EMGALITY prefilled syringe:
 | - Call your healthcare provider
 | - Call 1-800-LillyRx (1-800-545-5979)
 | - Visit www.emgality.com

Storing EMGALITY

- Store your prefilled syringe in the refrigerator between 36ºF to 46ºF (2ºC to 8ºC).

- Your prefilled syringe may be stored out of the refrigerator in the original carton at temperatures up to 86°F (30°C) for up to 7 days. After storing out of the refrigerator, do not place EMGALITY back in the refrigerator.

- Do not freeze your prefilled syringe.

- Keep your prefilled syringe in the carton it comes in to protect it from light until time of use.

- Do not shake your prefilled syringe.

- Throw away your prefilled syringe if any of the above conditions are not followed.

- Keep your prefilled syringe and all medicines out of the reach of children.

Read the full Prescribing Information and Patient Information for EMGALITY inside this box to learn more about your medicine.

Eli Lilly and Company

Indianapolis, IN 46285, USA

US License Number 1891

EMGALITY® is a registered trademark of Eli Lilly and Company.

Copyright © 2018, 2025, Eli Lilly and Company. All rights reserved.

This Instructions for Use has been approved by the U.S. Food and Drug Administration.

Revised: 11/2025

EMG-0005-PFS-120MG-IFU-20251119

INSTRUCTIONS FOR USE

EMGALITY® [em-GAL-it-ē]

(galcanezumab-gnlm)

injection, for subcutaneous use

Prefilled Syringe

This Instructions for Use contains information on how to inject EMGALITY

This Instructions for Use is for patients with episodic cluster headache.

- If you are using EMGALITY for preventive treatment of migraine, there is a different Instructions for Use because the dose and number of syringes needed is different.

For subcutaneous injection only.

Important Information You Need to Know Before Injecting EMGALITY

- Your healthcare provider or nurse should show you how to prepare and inject EMGALITY using the prefilled syringe. Do not inject yourself or someone else until you have been shown how to inject EMGALITY.

- Keep this Instructions for Use and refer to it as needed.

- Each EMGALITY prefilled syringe is for one-time use only. Do not share or reuse your EMGALITY prefilled syringe. You may give or get an infection.

- Your healthcare provider may help you decide where on your body to inject your dose. You can also read the “Choose your injection site” section of these instructions to help you choose which area can work best for you.

- If you have vision problems, do not use EMGALITY prefilled syringe without help from a caregiver.

- See “Storing EMGALITY” for important storage information.

INSTRUCTIONS FOR USE

Before you use the EMGALITY prefilled syringe, read and carefully follow all the step-by-step instructions.

Parts of the EMGALITY Prefilled Syringe

Step 1 Preparing to Inject EMGALITY

Step 1a Take the Prefilled Syringes from the refrigerator

Take 3 EMGALITY prefilled syringes from the refrigerator.

Check your prescription.

- EMGALITY comes as a single-dose prefilled syringe.
- You will need 3 prefilled syringes for each dose.

Leave the needle caps on until you are ready to inject.

Leave the prefilled syringes at room temperature for 30 minutes before injecting.

Do not microwave the prefilled syringes, run hot water over them, or leave them in direct sunlight.

Do not shake.

Step 1b Gather Supplies

For each injection you will need:

- 1 alcohol wipe
- 1 cotton ball or piece of gauze
- 1 sharps disposal container. See “After You Inject Your Medicine.”

Step 1c Inspect the Prefilled Syringe and the medicine

Make sure you have the right medicine. The medicine inside should be clear. Its color may be colorless to slightly yellow to slightly brown.

Do not use the prefilled syringe, and throw away (dispose of) as directed by your healthcare provider or pharmacist if:

- it looks damaged
- the medicine is cloudy, is discolored, or has small particles
- the Expiration Date (Exp.) printed on the label has passed (see Figure A)
- the medicine is frozen

Expiration Date
Figure A

Step 1d Prepare for injection

Wash your hands with soap and water before you inject your EMGALITY. Make sure a sharps disposal container is close by.

Step 1e Choose your injection site

Your healthcare provider can help you choose the injection site that is best for you.

Figure B

- You may inject the medicine into your stomach area (abdomen). Do not inject within 2 inches of the belly button (navel) (see Figure B).

- You may inject the medicine into the front of your thighs. This area should be at least 2 inches above the knee and 2 inches below the groin.

- Another person may give you the injection in the back of your upper arm or buttocks (see Figure B).

- Do not inject in the exact same spot. For example, if your first injection was in your abdomen, your next injection could be in another area of your abdomen.

- Do not inject into areas where the skin is tender, bruised, red, or hard.

- Clean your injection site with an alcohol wipe. Let the injection site dry before you inject.

Step 2 Injecting EMGALITY

Step 2a Uncap

Figure C

- Leave the needle cap on until you are ready to inject.

- Pull the needle cap off (see Figure C) and throw it away in your household trash.

- Do not put the needle cap back on. You could damage the needle or stick yourself by accident.

- Do not touch the needle.

Step 2b Insert

Figure D

- Gently pinch and hold a fold of skin where you will inject (see Figure D).

- Insert the needle at a 45-degree angle.

Step 2c Inject

Figure E

- Slowly push on the thumb pad to push the plunger all the way in until all the medicine is injected (see Figure E).

- The gray syringe plunger should be pushed all the way to the needle end of the syringe (see Figure F).

- You should see the coral plunger rod show through the syringe body when the injection is complete as shown (see Figure F).
- Remove the needle from your skin and gently let go of your skin.
- If you have bleeding at the injection site, press a cotton ball or gauze over the injection site. Do not rub the injection site.
- Do not put the needle cap back on the prefilled syringe.

Figure F

Step 3 Disposing of EMGALITY

Step 3a Throw away the used prefilled syringe

- Put the used EMGALITY prefilled syringe in an FDA-cleared sharps disposal container right away after use (see Figure G). Do not throw away (dispose of) the EMGALITY prefilled syringe in your household trash.

Figure G

- If you do not have an FDA-cleared sharps disposal container, you may use a household container that is:
  - made of a heavy-duty plastic,
  - can be closed with a tight-fitting, puncture-resistant lid, without sharps being able to come out,
  - upright and stable during use,
  - leak-resistant, and
  - properly labeled to warn of hazardous waste inside the container.
- When your sharps disposal container is almost full, you will need to follow your community guidelines for the right way to dispose of your sharps disposal container. There may be state or local laws about how you should throw away needles and syringes. For more information about safe sharps disposal, and for specific information about sharps disposal in the state you live in, go to the FDA's website at: http://www.fda.gov/safesharpsdisposal.
- Do not recycle your used sharps disposal container.

For each of the 3 injections, repeat all instructions with a new prefilled syringe.

Commonly Asked Questions
Q. | What if I see air bubbles in my EMGALITY prefilled syringe?
A. | It is normal to have air bubbles in the prefilled syringe. EMGALITY is injected under your skin (subcutaneous injection), so these air bubbles will not harm you.
Q. | What if there is a drop of liquid on the tip of the needle when I remove the needle cap?
A. | It is okay to see a drop of liquid on the tip of the needle.
Q. | What if I cannot push in the plunger?
A. | If the plunger is stuck or damaged:
 | - Do not continue to use the syringe
 | - Remove the needle from your skin
 | - Dispose of the syringe and get a new one
Q. | What if there is a drop of liquid or blood on my skin after my injection?
A. | This is normal. Press a cotton ball or gauze over the injection site. Do not rub the injection site.
Q. | How can I tell if my injection is complete?
A. | When your injection is complete:
 | - The coral plunger rod should show through the body of the syringe.
 | - The gray syringe plunger should be pushed all the way to the needle end of the syringe.
If you have more questions about how to use the EMGALITY prefilled syringe:
 | - Call your healthcare provider
 | - Call 1-800-LillyRx (1-800-545-5979)
 | - Visit www.emgality.com

Storing EMGALITY

- Store your prefilled syringes in the refrigerator between 36ºF to 46ºF (2ºC to 8ºC).

- Your prefilled syringes may be stored out of the refrigerator in the original carton at temperatures up to 86ºF (30ºC) for up to 7 days. After storing out of the refrigerator, do not place EMGALITY back in the refrigerator.

- Do not freeze your prefilled syringes.

- Keep your prefilled syringes in the carton they come in to protect them from light until time of use.

- Do not shake your prefilled syringes.

- Throw away your prefilled syringes if any of the above conditions are not followed.

- Keep your prefilled syringes and all medicines out of the reach of children.

Read the full Prescribing Information and Patient Information for EMGALITY inside this box to learn more about your medicine.

Eli Lilly and Company

Indianapolis, IN 46285, USA

US License Number 1891

EMGALITY® is a registered trademark of Eli Lilly and Company.

Copyright © 2019, 2025, Eli Lilly and Company. All rights reserved.

This Instructions for Use has been approved by the U.S. Food and Drug Administration.
Revised: 11/2025

EMG-0002-PFS-100MG-IFU-20251119

PACKAGE CARTON – EMGALITY Autoinjector 120 mg

NDC 0002-1436-11

EMGALITY®

(galcanezumab-gnlm) injection

120 mg/mL

1 x 120 mg/mL Single-Dose prefilled pen

For Subcutaneous Use Only

Single-Dose Only

Rx only

Lilly

PACKAGE CARTON – EMGALITY Prefilled Syringe 120 mg

NDC 0002-2377-11

EMGALITY®

(galcanezumab-gnlm) injection

120 mg/mL

1x 120 mg/mL Single-Dose prefilled syringe

For Subcutaneous Use Only

Single-Dose Only

Rx only

Lilly

PACKAGE CARTON – EMGALITY Prefilled Syringe 100 mg

NDC 0002-3115-09

EMGALITY®

(galcanezumab-gnlm)

100 mg/mL injection

All 3 syringes must be administered to receive the 300 mg dose.

3 x 100 mg/mL Single-Dose prefilled syringe

For Subcutaneous Use Only

Single-Dose Only

Rx only

Lilly